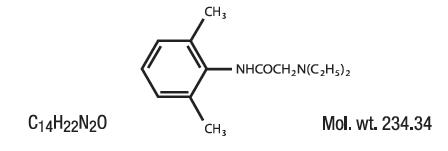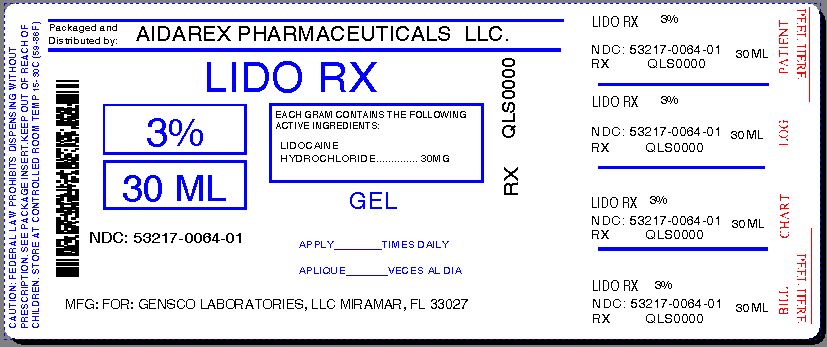 DRUG LABEL: Lidocaine Hydrochloride
NDC: 53217-064 | Form: GEL
Manufacturer: Aidarex Pharmaceuticals LLC
Category: prescription | Type: HUMAN PRESCRIPTION DRUG LABEL
Date: 20140109

ACTIVE INGREDIENTS: LIDOCAINE 30 mg/1 g
INACTIVE INGREDIENTS: WATER; CARBOMER COPOLYMER TYPE B (ALLYL PENTAERYTHRITOL CROSSLINKED); ISOPROPYL ALCOHOL; PETROLATUM; POLYSORBATE 20; TROLAMINE

LidoRx (Lidocaine HCl USP) 3%

Rx only

DO NOT USE IN THE EYES.

DESCRIPTION

Lidocaine HCL USP, 3% contains a local anesthetic agent and is administered topically. See INDICATIONS AND USAGE for specific uses.

Lidocaine HCL USP, 3% contains lidocaine, which is chemically designated as acetamide, 2-(diethylamino)-N-(2,6-dimethylphenyl)-, and has the following structural formula:

Composition of Lidocaine HCL USP, 3%: Each gram contains lidocaine hydrocloride USP, 3% in a water soluble base containing AQUA (DEIONIZED WATER), CARBOMER, ISOPROPYL ALCOHOL, PETROLATUM, POLYSORBATE-20, TRIETHANOLAMINE.

CLINICAL PHARMACOLOGY

MECHANISM OF ACTION

LidoRx 3% releases Lidocaine Hydrochloride USP from a mild acidic vehicle to stabilize the neuronal membrane by inhibiting the ionic fluxes required for initiation and conduction of impulses, thereby effecting local anesthetic action. A mild acidic vehicle lowers pH to increase protection against alkaline irritations and to provide a favorable environment for healing.

Onset of anesthesia

LidoRx 3% effects local, topical anesthesia. The onset of action is 3-5 minutes.

Hemodynamics

Excessive blood levels may cause changes in cardiac output, total peripheral resistance, and mean arterial pressure. These changes may be attributable to a direct depressant effect of the local anesthetic agent on various components of the cardiovascular system.

Pharmacokinetics and metabolism

Lidocaine Hydrochloride USP may be absorbed following topical administration to mucous membranes or open wounds, its rate and extent of absorption depending upon the specific site of application, duration of exposure, concentration, and total dosage. In general, the rate of absorption of local anesthetic agents following topical application occurs most rapidly after intratracheal administration. Lidocaine Hydrochloride USP is also well-absorbed from the gastrointestinal tract, but little intact drug appears in the circulation because of biotransformation in the liver.

Lidocaine Hydrochloride USP is metabolized rapidly by the liver, and metabolites and unchanged drug are excreted by the kidneys. Biotransformation includes oxidative N-dealkylation, ring hydroxylation, cleavage of the amide linkage, and conjugation. N-dealkylation, a major pathway of biotransformation, yields the metabolites monoethylglycinexylidide and glycinexylidide. The pharmacological/toxicological actions of these metabolites are similar to, but less potent than, those of Lidocaine Hydrochloride USP. Approximately 90% of Lidocaine Hydrochloride USP administered is excreted in the form of various metabolites, and less than 10% is excreted unchanged. The primary metabolite in urine is a conjugate of 4-hydroxy-2,6-dimethylaniline.

The plasma binding of Lidocaine Hydrochloride USP is dependent on drug concentration, and the fraction bound decreases with increasing concentration. At concentrations of 1 to 4 μg of free base per mL, 60 to 80 percent of Lidocaine Hydrochloride USP is protein bound. Binding is also dependent on the plasma concentration of the alpha-l-acid glycoprotein.

Lidocaine crosses the blood-brain and placental barriers, presumably by passive diffusion.

Studies of Lidocaine Hydrochloride USP metabolism following intravenous bolus injections have shown that the elimination half-life of this agent is typically 1.5 to 2.0 hours. Because of the rapid rate at which Lidocaine Hydrochloride USP is metabolized, any condition that affects liver function may alter Lidocaine Hydrochloride USP kinetics.

The half-life may be prolonged two-fold or more in patients with liver dysfunction. Renal dysfunction does not affect Lidocaine Hydrochloride USP kinetics but may increase the accumulation of metabolites.

Factors such as acidosis and the use of CNS stimulants and depressants affect the CNS levels of Lidocaine Hydrochloride USP required to produce overt systemic effects. Objective adverse manifestations become increasingly apparent with increasing venous plasma levels above 6.0 μg free base per mL. In the rhesus monkey arterial blood levels of 18-21 μg/mL have been shown to be threshold for convulsive activity.

INDICATIONS AND USAGE

Anesthetic for relief of pruritus, pruritic eczemas, abrasions, minor burns, insect bites, pain, soreness and discomfort due to pruritus ani, pruritus vulvae,hemorrhoids, anal fissures, and similar conditions of the skin and mucous membranes.

CONTRAINDICATIONS

Lidocaine Hydrochloride USP is contraindicated in patients with a known history of hypersensitivity to local anesthetics of the amide type or to other components of LidoRx 3%.

Do not use LidoRx 3% on traumatized mucosa or in the presence of secondary bacterial infection of the area of proposed application.

WARNINGS

EXCESSIVE DOSAGE, OR SHORT INTERVALS BETWEEN DOSES, CAN RESULT IN HIGH PLASMA LEVELS AND SERIOUS ADVERSE EFFECTS. PATIENTS SHOULD BE INSTRUCTED TO STRICTLY ADHERE TO THE RECOMMENDED DOSAGE AND ADMINISTRATION GUIDELINES AS SET FORTH IN THIS PACKAGE INSERT.

THE MANAGEMENT OF SERIOUS ADVERSE REACTIONS MAY REQUIRE THE USE OF RESUSCITATIVE EQUIPMENT, OXYGEN, AND OTHER RESUSCITATIVE DRUGS.

LidoRx 3% should be used with extreme caution in the presence of sepsis or severely traumatized mucosa in the area of application, since under such conditions there is the potential for rapid systemic absorption.

For external use only. Not for ophthalmic use.
Keep out of reach of children.

PRECAUTIONS

If irritation or sensitivity occurs or infection appears, discontinue use and institute appropriate therapy. LidoRx 3% Gel should be used with caution in ill, elderly, debilitated patients and children who may be more sensitive to the systemic effects of Lidocaine Hydrochloride USP. In case of accidental ingestion get medical help or contact poison control center right away.

CARCINOGENESIS, MUTAGENESIS, AND IMPAIRMENT OF FERTILITY

Studies of lidocaine in animals to evaluate the carcinogenic potential of the effect on fertility have not been conducted.

USE IN PREGNANCY

Teratogenic Effects:

Teratogenic Effects. Pregnancy Category B. Reproduction studies have been performed in rats at doses up to 6.6 times the human dose and have revealed no evidence of harm to the fetus caused by Lidocaine Hydrochloride USP. There are, however, no adequate and well-controlled studies in pregnant women. Animal reproduction studies are not always predictive of human response. General consideration should be given to this fact before administering Lidocaine Hydrochloride USP to women of childbearing potential, especially during early pregnancy when maximum organogenesis takes place.

NURSING MOTHERS:

It is not known whether this drug is excreted in human milk. Because many drugs are excreted in human milk, caution should be exercised when Lidocaine Hydrochloride USP. is administered to a nursing woman.

PEDIATRIC USE:

Dosage in children should be reduced, commensurate with age, body weight and physical condition. Caution must be taken to avoid over dosage when applying LidoRx 3% to large areas of injured or abraded skin, since the systemic absorption of Lidocaine Hydrochloride USP may be increased under such conditions.

ADVERSE REACTIONS:

Adverse experiences following the administration of Lidocaine Hydrochloride USP are similar in nature to those observed with other amide local anesthetic agents. These adverse experiences are, in general, dose-related and may result from high plasma levels caused by excessive dosage or rapid absorption, or may result from a hypersensitivity, idiosyncrasy or diminished tolerance on the part of the patient.
Serious adverse experiences are generally systemic in nature. The following types are those most commonly reported:

Central Nervous System:

CNS manifestations are excitatory and/or depressant and may be characterized by lightheadedness, nervousness, apprehension, euphoria, confusion, dizziness, drowsiness, tinnitus, blurred or double vision, vomiting, sensations of heat, cold or numbness, twitching, tremors, convulsions, unconsciousness, respiratory depression and arrest. The excitatory manifestations may be very brief or may not occur at all, in which case the first manifestation of toxicity may be drowsiness merging into unconsciousness and respiratory arrest. Drowsiness following the administration of lidocaine is usually an early sign of a high blood level of the drug and may occur as a consequence of rapid absorption.

Cardiovascular system

Cardiovascular manifestations are usually depressant and are characterized by bradycardia, hypotension, and cardiovascular collapse, which may lead to cardiac arrest.

Allergic

Allergic reactions are characterized by cutaneous lesions, urticaria, edema or anaphylactoid reactions. Allergic reactions may occur as a result of sensitivity either to the local anesthetic agent or to other components in the formulation. Allergic reactions as a result of sensitivity to lidocaine are extremely rare and, if they occur, should be managed by conventional means. The detection of sensitivity by skin testing is of doubtful value.

DOSAGE AND ADMINISTRATION:

Each pump of the LidoRx 3% bottle in 30mL Airless Pumps (NDC:35781-0300-3) will deliver 0.25 mL of LidoRx 3% enough to cover a 2 x 2 inch area of skin. A single application should not exceed 10 g of LidoRx 3%, containing 300 mg of Lidocaine Hydrochloride USP; This would equal 40 pumps of the 30mL Airless bottle. In a 70 kg adult this dose equals 4.3 mg/kg (1.9 mg/lb) Lidocaine Hydrochloride USP. No more than one 30mL Airless Pump bottle, approximately 30g of LidoRx 3% or 900 mg Lidocaine Hydrochloride USP, should be administered in any one day.
Although the incidence of adverse effects with LidoRx 3% is quite low, caution should be exercised, particularly when employing large amounts, since the incidence of adverse effects is directly proportional to the total dose of local anesthetic agent administered.

Dosage for children:

It is difficult to recommend a maximum dose of any drug for children since this varies as a function of age and weight. For children less than ten years who have a normal lean body mass and a normal lean body development, the maximum dose may be determined by the application of one of the standard pediatric drug formulas (e.g., Clark’s rule). For example a child of five years weighing 50 lbs., the dose of lidocaine should not exceed 75-100 mg when calculated according to Clark’s rule. In any case, the maximum amount of Lidocaine Hydrochloride USP administered should not exceed 4.3 mg/kg (2.0 mg/lb) of body weight.

Administration

Apply a thin film to the affected area two or three times daily not to exceed 12 pumps in twenty four hours (24Hrs). One pump covers an area of 2 x2 inches. Larger areas will require additional applications. Or use as directed by a physician.

STORAGE AND HANDLING

All prescriptions using this product shall be pursuant to state statutes as applicable. This product may be administered only under a physician’s supervision. There are no implied or explicit claims on the therapeutic equivalence.
Store at 25ºC (77ºF); excursions permitted to 15º-30ºC (59º-86º F). See USP Controlled Room Temperature. Protect from freezing.

HOW SUPPLIED

Lido Rx 3%(Lidocaine HCl USP 3%)

1.01 oz (28.5g) 30mL Airless Pump - NDC 53217-0064-01

Gensco Labratories, LLC
12741 Miramar Parkway
Miramar, FL 33027

Repackaged By :
Aidarex Pharmaceuticals LLC,
Corona, CA 92880